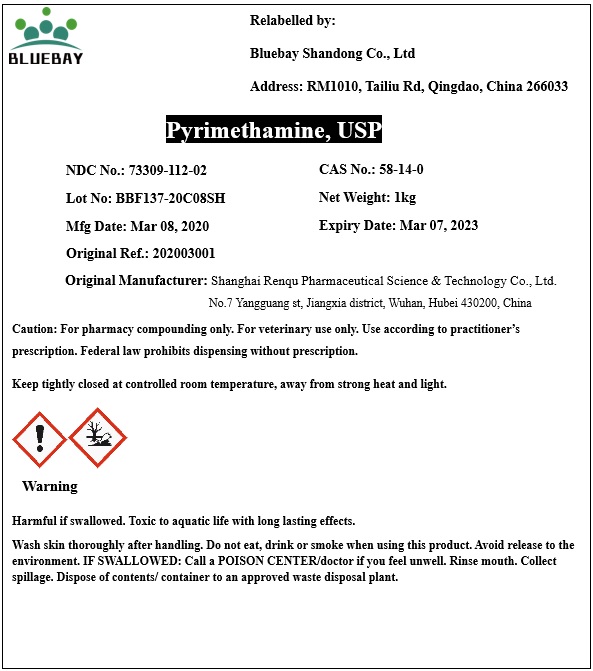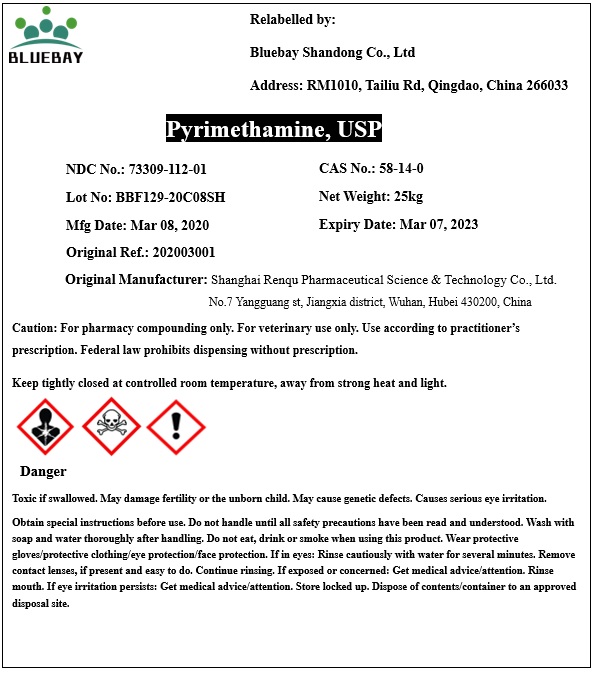 DRUG LABEL: Pyrimethamine
NDC: 73309-112 | Form: POWDER
Manufacturer: BLUEBAY SHANDONG CO.,LTD
Category: other | Type: BULK INGREDIENT
Date: 20200403

ACTIVE INGREDIENTS: PYRIMETHAMINE 1 kg/1 kg

Pyrimethamine